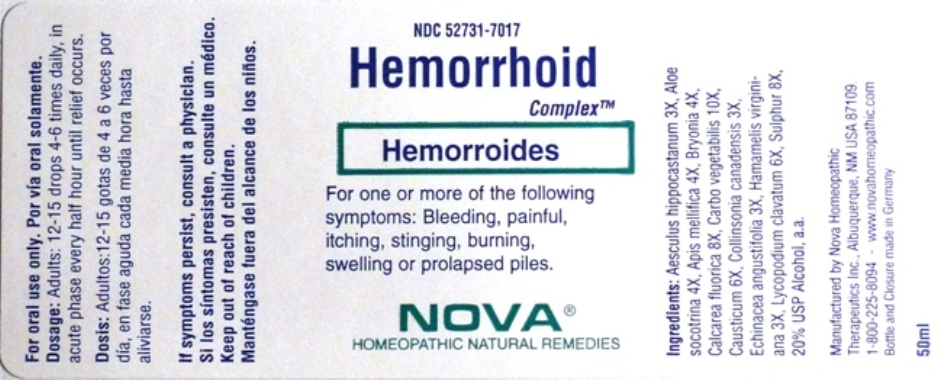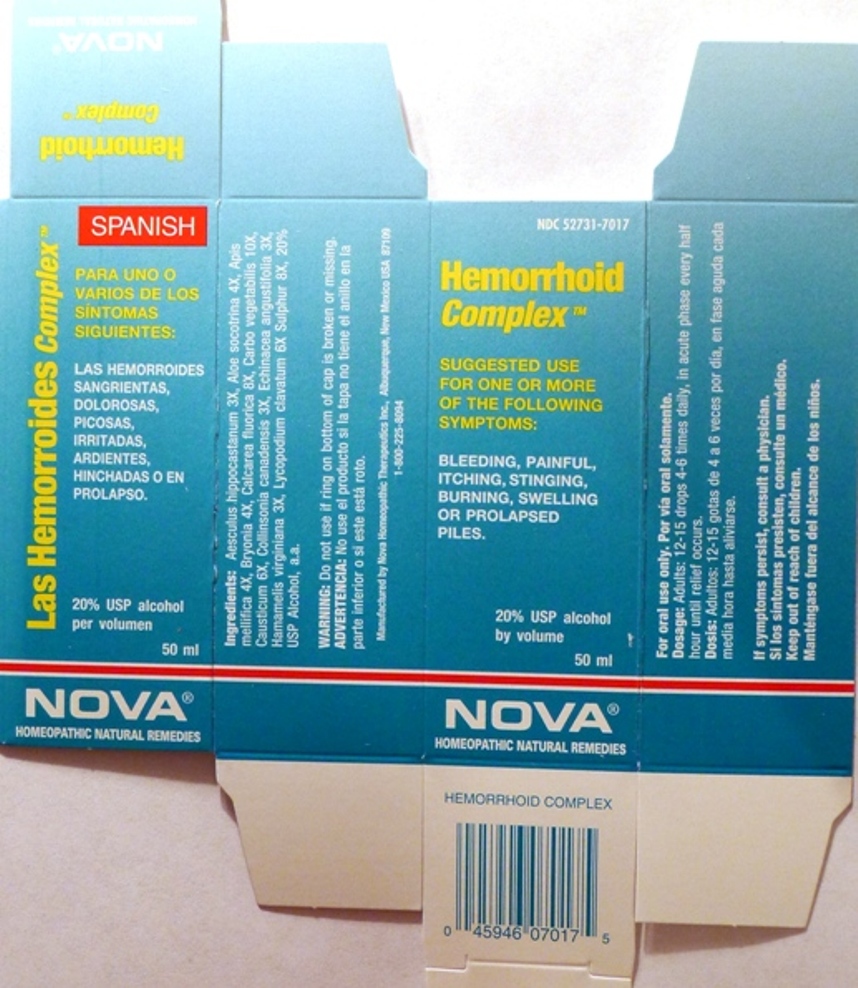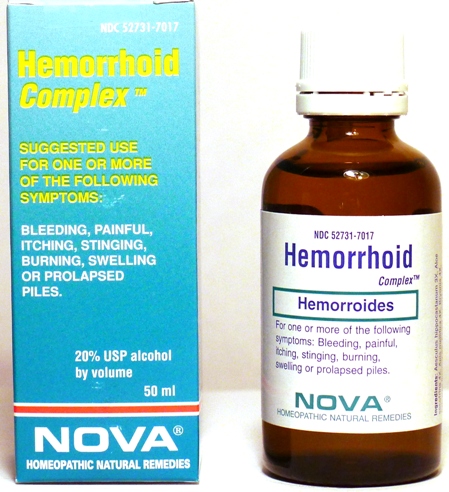 DRUG LABEL: Hemorrhoid Complex
NDC: 52731-7017 | Form: LIQUID
Manufacturer: Nova Homeopathic Therapeutics, Inc.
Category: homeopathic | Type: HUMAN OTC DRUG LABEL
Date: 20110601

ACTIVE INGREDIENTS: HORSE CHESTNUT 3 [hp_X]/1 mL; ALOE 4 [hp_X]/1 mL; APIS MELLIFERA 4 [hp_X]/1 mL; BRYONIA ALBA ROOT 4 [hp_X]/1 mL; CALCIUM FLUORIDE 8 [hp_X]/1 mL; ACTIVATED CHARCOAL 10 [hp_X]/1 mL; CAUSTICUM 6 [hp_X]/1 mL; COLLINSONIA CANADENSIS ROOT 3 [hp_X]/1 mL; ECHINACEA ANGUSTIFOLIA 3 [hp_X]/1 mL; HAMAMELIS VIRGINIANA ROOT BARK/STEM BARK 3 [hp_X]/1 mL; LYCOPODIUM CLAVATUM SPORE 6 [hp_X]/1 mL; SULFUR 8 [hp_X]/1 mL
INACTIVE INGREDIENTS: ALCOHOL

Hemorrhoid Complex

Purpose:

Suggested use for one or more of the following symptoms:

Bleeding, painful, itching, stinging, burning, swelling or prolapsed piles.

Usage and Dosage:

For oral use only.

DOSAGE AND ADMINISTRATION

Adults:
In Acute Phase:
12-15 drops, every half hour until relief occurs
When Relief Occurs:
12-15 drops, 4-6 times per day

Warnings:

Keep out of reach of children.

WARNINGS

If symptoms persist, consult a physician.
Do not use if ring on bottom of cap is broken or missing.

Active Ingredients:

Aesculus hippocastanum 3X, Aloe socotrina 4X, Apis mellifica 4X, Bryonia 4X, Calcarea fluorica 8X, Carbo vegetabilis 10X, Causticum 6X, Collinsonia canadensis 3X, Echinacea angustifolia 3X, Hamamelis virginiana 3X, Lycopodium clavatum 6X Sulphur 8X

Inactive Ingredients:

Alcohol, 20% USP

QUESTIONS

Manufactured by Nova Homeopathic Therapeutics Inc., Albuquerque, New Mexico USA 87109
1-800-225-8094

PACKAGE LABEL

Hemorrhoid Complex Product

Hemorrhoid Complex Bottle Label

Hemorrhoid Complex Box